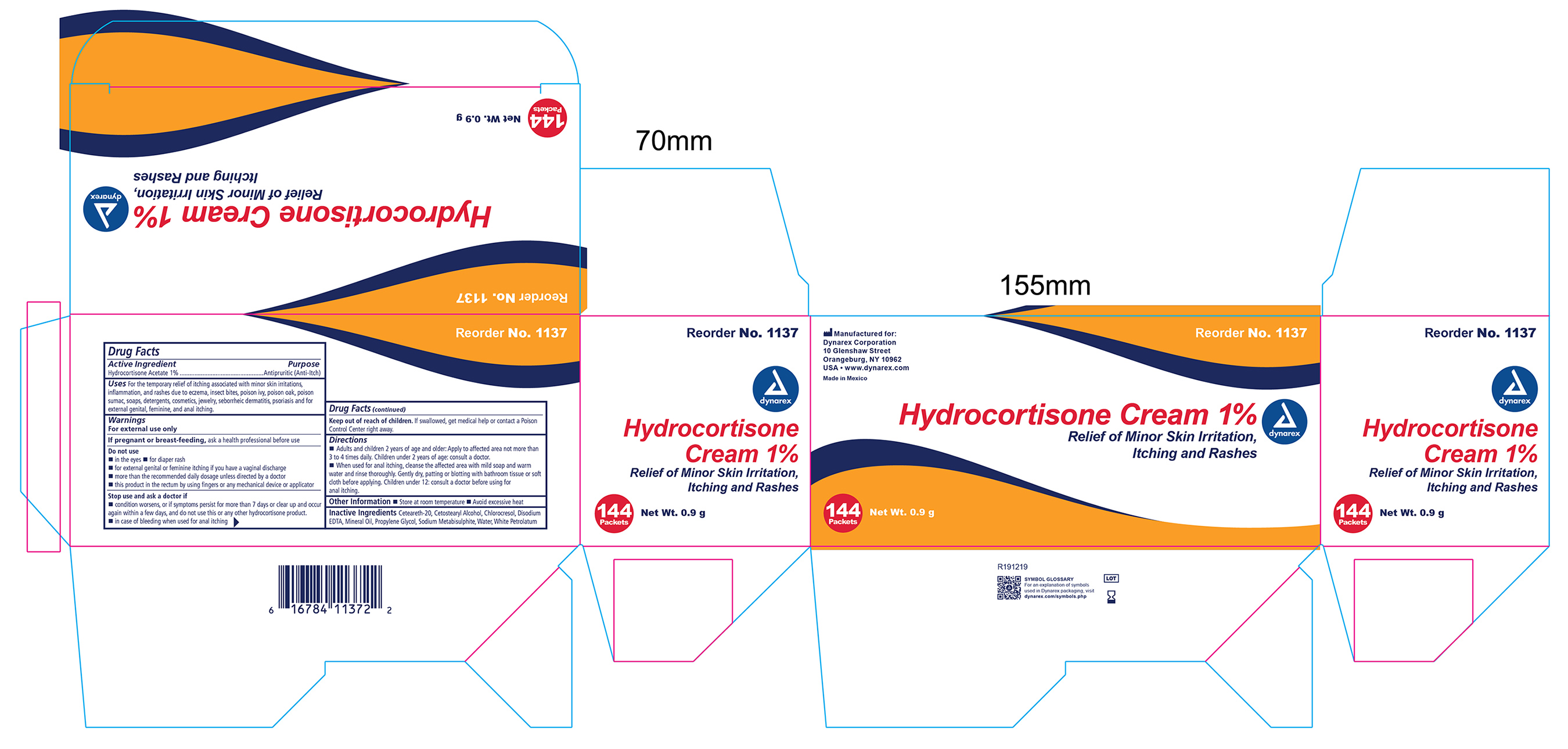 DRUG LABEL: Hydrocortisone
NDC: 67777-003 | Form: CREAM
Manufacturer: Dynarex Corporation
Category: otc | Type: HUMAN OTC DRUG LABEL
Date: 20241120

ACTIVE INGREDIENTS: HYDROCORTISONE ACETATE 1 g/100 g
INACTIVE INGREDIENTS: POLYOXYL 20 CETOSTEARYL ETHER; MINERAL OIL; CETOSTEARYL ALCOHOL; CHLOROCRESOL; EDETATE DISODIUM ANHYDROUS; PROPYLENE GLYCOL; SODIUM METABISULFITE; WATER; PETROLATUM

1137 Hydrocortisone Cream NDC 67777-003-01

Active Ingredient

Hydrocortisone Acetate 1%

Purpose

Antipruritic (Anti-Itch)

Uses

For temporary relief of itching associated with minor skin irritations, inflammation, and rashes due to eczema, insect bites, poison ivy, poison oak, poison sumac, soaps, detergents, cosmetics, jewelry, seborrheic dermatitis, psoriasis and for external genital, feminine, and anal itching.

Warnings

For external use only

If pregnant or breast-feeding,

ask a health professional before use

Do not use

- in the yes
- for diaper rash
- for external genital or feminine itching if you have a vaginal discharge
- more than the recommended daily dosage unless directed by a doctor
- this product in the rectumby using fingers or any mechanical device or applicator

Stop use and ask a doctor if

- condition worsens, or if symptoms persist for more than 7 days or clear up and occur again within a few days, and do not use this or any other hydrocortisone product.
- in case of bleeding when used for anal itching

KEEP OUT OF REACH OF CHILDREN

If swallowed, get medical help or contact a Poison Control Center right away.

Directions

- Adults and children 2 years of age and older: Apply to affected area not more than 3 to 4 time daily. Children under 2 years of age: consult a doctor.
- When used for anal itching, cleanse the affected area with mild soap and warm water and rinse thoroughly. Gently dry, patting or blotting with bathroom tissue or soft cloth before applying. Children under 12: consult a doctor before using for anal itching.

Other Information

- Store at room temperature
- Avoid excessive heat

Inactive Ingredients

Ceteareth-20, Cetostearyl Alcohol, Chlorocresol, Disodium EDTA, Mineral Oil, Propylene Glycol, Sodium Metabisulfite, Water, White Petrolatum